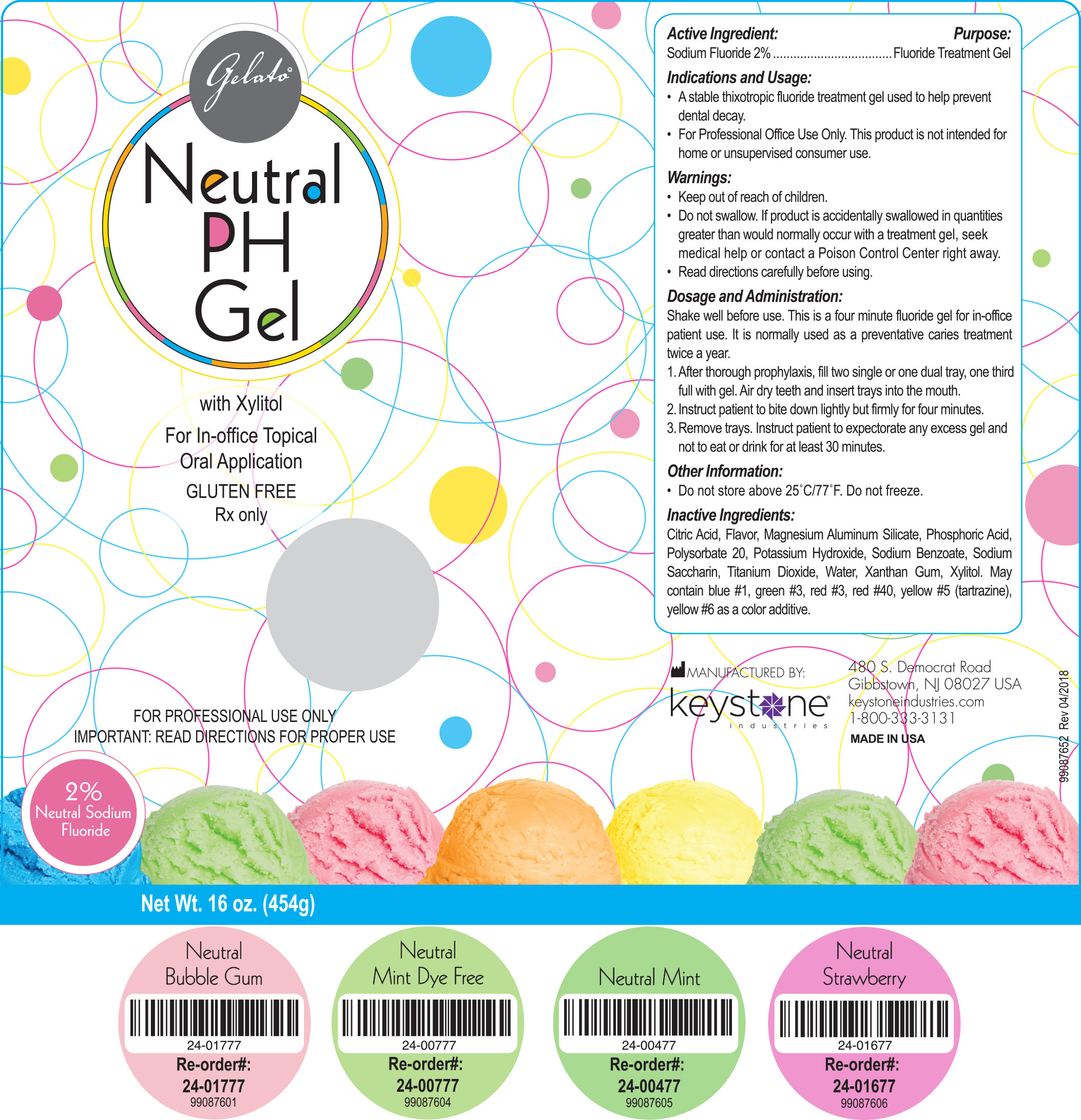 DRUG LABEL: Gelato Neutral pH
NDC: 68400-324 | Form: GEL
Manufacturer: Mycone Dental Supply Co., Inc DBA Keystone Industries and Deepak Products Inc
Category: prescription | Type: HUMAN PRESCRIPTION DRUG LABEL
Date: 20240422

ACTIVE INGREDIENTS: SODIUM FLUORIDE 4.086 g/454 g
INACTIVE INGREDIENTS: CITRIC ACID MONOHYDRATE; MAGNESIUM ALUMINUM SILICATE; PHOSPHORIC ACID; POLYSORBATE 20; POTASSIUM HYDROXIDE; SODIUM BENZOATE; SACCHARIN SODIUM; TITANIUM DIOXIDE; WATER; XANTHAN GUM; XYLITOL; FD&C BLUE NO. 1; FD&C GREEN NO. 3; FD&C RED NO. 3; FD&C RED NO. 40; FD&C YELLOW NO. 5; FD&C YELLOW NO. 6

Active Ingredient:

Sodium Fluoride 2%

Purpose:

Fluoride Treatment Gel

Indications and Usage:

- A stable thixotropic fluoride treatment gel used to help prevent dental decay.
- For Professional Office Use Only. This product is not intended for home or unsupervised consumer use.

Warnings:

- Keep out of reach of children.
- Do not swallow. If product is accidentally swallowed in quantities greater than would normally occur with a treatment gel, seek medical help or contact a Poison Control Center right away.
- Read directions carefully before using.

Dosage and Administration:

Shake well before use. This is a four minute fluoride gel for in-office patient use. It is normally used as a preventative caries treatment twice a year.

1. After thorough prophylaxis, fill two single or one dual tray, one third full with gel. Air dry teeth and insert trays into the mouth.

2. Instruct patient to bite down lightly but firmly for four minutes.

3. Remove trays. Instruct patient to expectorate any excess gel and not to eat or drink for at least 30 minutes.

Other Infomation:

- Do not store above 25°C/77°F. Do not freeze.

Inactive Ingredients:

Citric Acid, Flavor, Magnesium Aluminum Silicate, Phosphoric Acid, Polysorbate 20, Potassium Hydroxide, Sodium Benzoate, Sodium Saccharin, Titanium Dioxide, Water, Xanthan Gum, Xylitol. May contain blue #1, green #3, red #3, red #40, yellow #5 (tartrazine), yellow #6 as a color additive.